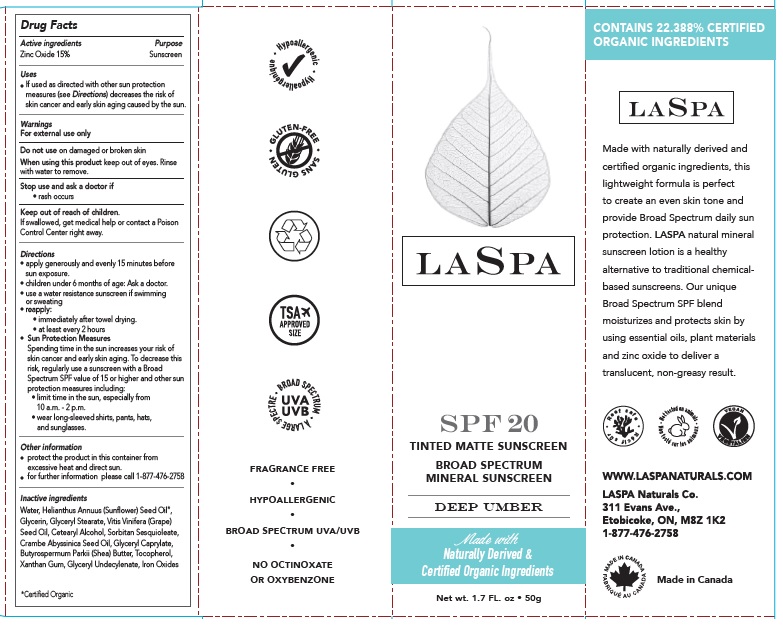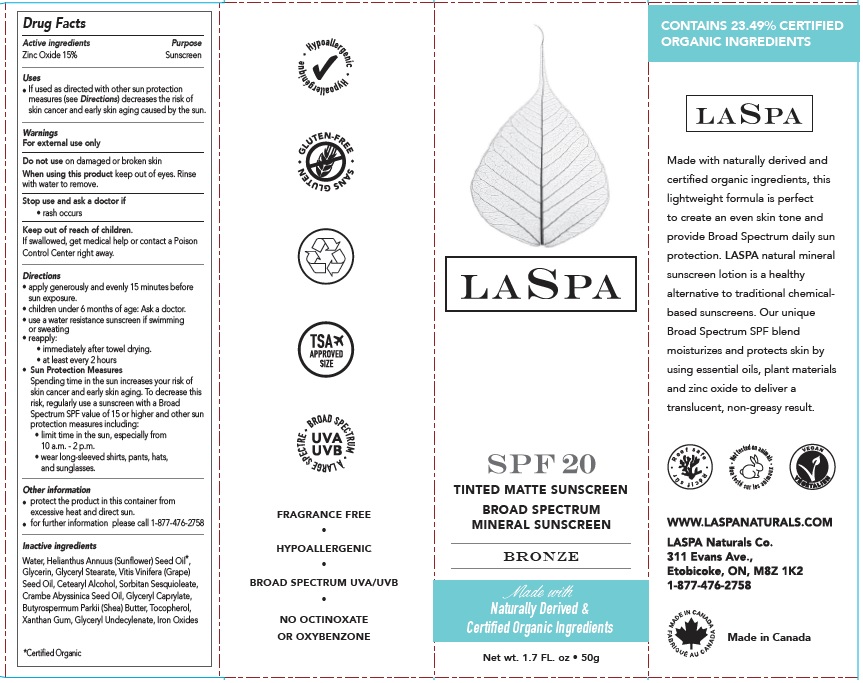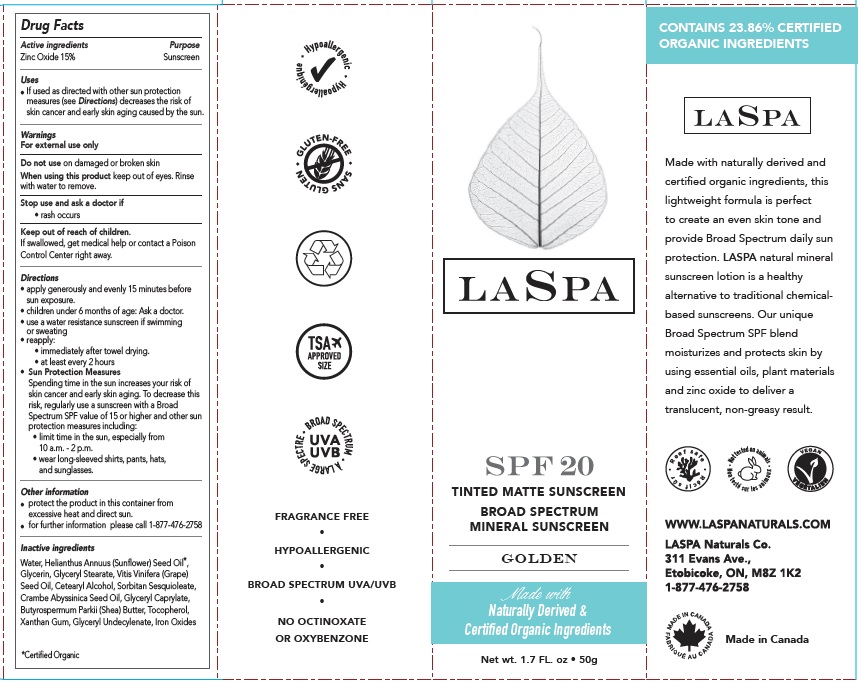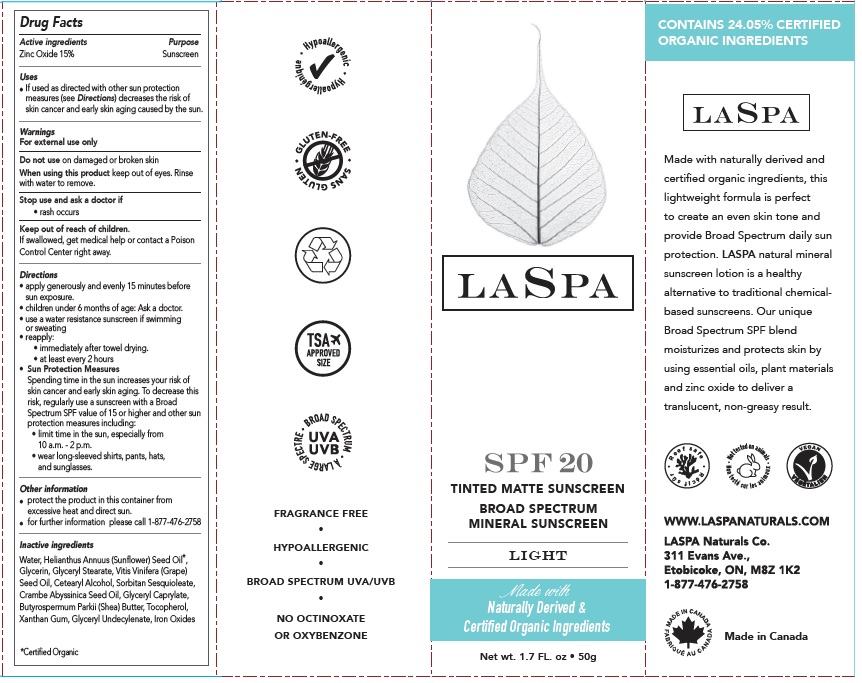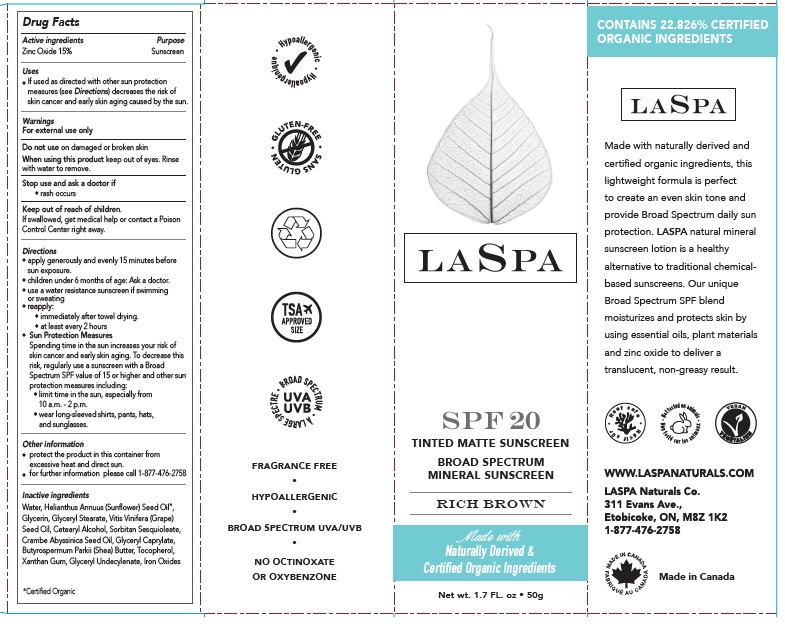 DRUG LABEL: LASPA TINTED MATTE SUNSCREEN SPF 20 GOLDEN
NDC: 71780-521 | Form: LOTION
Manufacturer: The Green Cricket Inc
Category: otc | Type: HUMAN OTC DRUG LABEL
Date: 20211011

ACTIVE INGREDIENTS: ZINC OXIDE 150 mg/1 g
INACTIVE INGREDIENTS: CRAMBE HISPANICA SUBSP. ABYSSINICA SEED OIL; GLYCERYL CAPRYLATE; FERRIC OXIDE RED; FERRIC OXIDE YELLOW; TOCOPHEROL; XANTHAN GUM; SUNFLOWER OIL; GLYCERYL MONOSTEARATE; SORBITAN SESQUIOLEATE; GLYCERIN; SHEA BUTTER; WATER; CETOSTEARYL ALCOHOL; BROWN IRON OXIDE; GRAPE SEED OIL; GLYCERYL 1-UNDECYLENATE

LASPA TINTED MATTE SUNSCREEN SPF 20

Active ingredient

Zinc Oxide 15%

Purpose

Sunscreen

Uses

- If used as directed with other sun protection measures (see Directions) decreases the risk of skin cancer and early skin aging caused by the sun.

Warnings

For external use only

Do not use

on damaged or broken skin

When using this product

keep out of eyes. Rinse with water to remove.

Stop use and ask a doctor if

rash occurs

Keep out of reach of children.

If swallowed, get medical help or contact a Poison Control Center right away.

Directions

- apply generously and evenly 15 minutes before sun exposure.
- children under 6 months of age: Ask a doctor.
- use a water resistance sunscreen if swimming or sweating
- reapply:
- immediately after towel drying.
- at least every 2 hours
- Sun Protection Measures: Spending time in the sun increases your risk of skin cancer and early skin aging. To decrease this risk, regularly use a sunscreen with a Broad Spectrum SPF value of 15 or higher and other sun protection measures including:
- limit time in the sun, especially from 10 a.m. - 2 p.m.
- wear long-sleeved shirts, pants, hats, and sunglasses.

Other information

- protect the product in this container from excessive heat and direct sun.
- for further information please call 1-877-476-2758

Inactive ingredients

Water, Helianthus Annuus (Sunflower) Seed Oil*, Glycerin, Glyceryl Stearate, Vitis Vinifera (Grape) Seed OIl, Cetearyl Alcohol, Sorbitan Sesquioleate, Crambe Abyssinica Seed Oil, Glyceryl Caprylate, Butyrospermum Parkii (Shea) Butter, Tocopherol, Xanthan Gum, Glyceryl Undecylenate, Iron Oxides

*Certified Organic

Company Information

LASPA Naturals Co.

311 Evans Ave.,

Etobicoke, ON, M8Z 1K2

1-877-476-2758